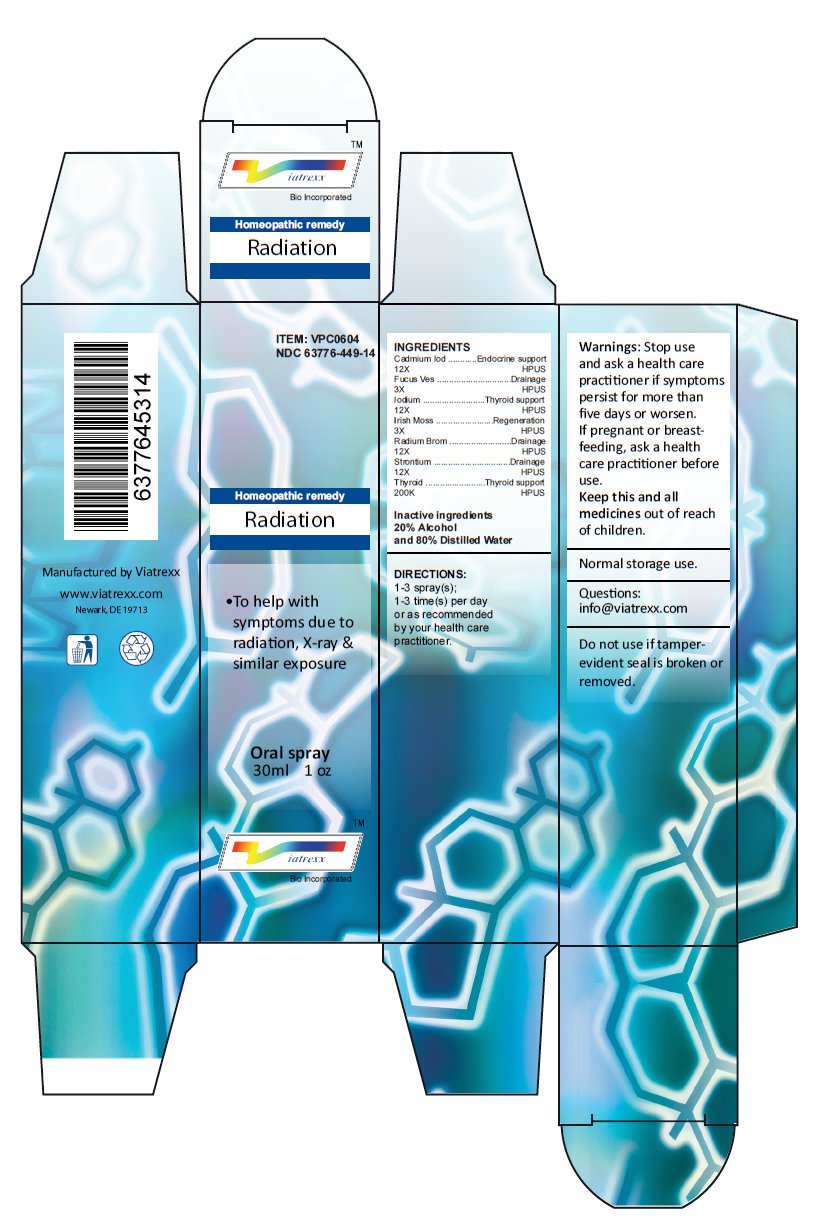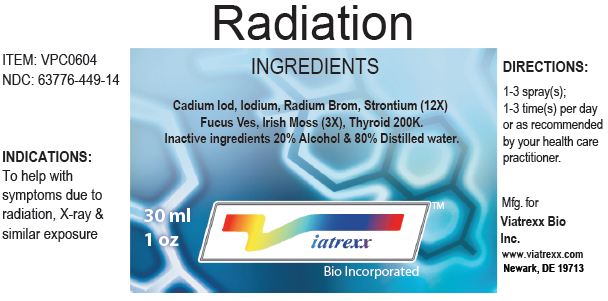 DRUG LABEL: Radiation
NDC: 63776-449 | Form: SPRAY
Manufacturer: VIATREXX BIO INCORPORATED
Category: homeopathic | Type: HUMAN OTC DRUG LABEL
Date: 20230110

ACTIVE INGREDIENTS: CADMIUM IODIDE 12 [hp_X]/1 mL; FUCUS VESICULOSUS 3 [hp_X]/1 mL; IODINE 12 [hp_X]/1 mL; CHONDRUS CRISPUS 3 [hp_X]/1 mL; RADIUM BROMIDE 12 [hp_X]/1 mL; STRONTIUM 12 [hp_X]/1 mL; THYROID, BOVINE 200 [kp_C]/1 mL; THYROID, PORCINE 200 [kp_C]/1 mL
INACTIVE INGREDIENTS: ALCOHOL; WATER

Radiation

Active Ingredients

Cadmium Iod 12X, Fucus Ves 3X, Iodium 12X, Irish Moss 3X, Radium Brom 12X, Strontium 12X, Thyroid 200K

Purpose

Cadmium Iod | Endocrine support
Fucus Ves | Drainage
Iodium | Thyroid support
Irish Moss | Regeneration
Radium Brom | Drainage
Strontium | Drainage
Thyroid | Thyroid support

Uses

To help with symptoms due to radiation, X-ray & similar exposure

Warnings

Stop use and ask a health care practitioner if symptoms persist for more than five days or worsen. If pregnant or breastfeeding, ask a health care practitioner before use.

Dosage

1-3 spray(s); 1-3 time(s) per day or as recommended by your healthcare practitioner.

KEEP OUT OF REACH OF CHILDREN

Keep this and all medicines out of reach of children.

Other Ingredients

Alcohol and Water

Other Information

Normal storage use.
Do not use if tamper-evident seal is broken or removed.

Questions

info@viatrexx.com

Principal Display Panel

ITEM: VPC0604
NDC 63776-449-14
Homeopathic remedy
Radiation
• To help with symptoms due to radiation, X-ray & similar exposure
Oral spray
30ml 1 oz
Viatrexx™ Bio Incorporated
Manufactured by Viatrexx
www.viatrexx.com
Newark, DE 19713

Radiation
30 mL
1 oz
Viatrexx™ Bio Incorporated
ITEM: VPC0604
NDC: 63776-449-14
INDICATIONS:
To help with symptoms due to radiation, X-ray & similar exposure
DIRECTIONS:
1-3 spray(s); 1-3 time(s) per day or as recommended by your health care practitioner.
Mfg. for
Viatrexx Bio Inc.
www.viatrexx.com
Newark, DE 19713